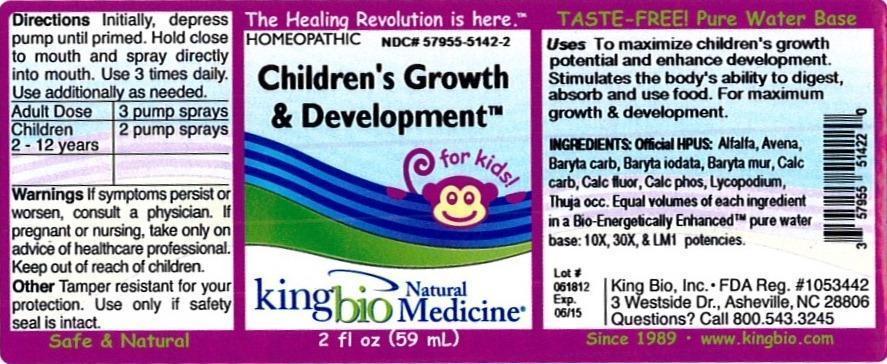 DRUG LABEL: Childrens Growth and Development
NDC: 57955-5142 | Form: LIQUID
Manufacturer: King Bio Inc.
Category: homeopathic | Type: HUMAN OTC DRUG LABEL
Date: 20120822

ACTIVE INGREDIENTS: ALFALFA 10 [hp_X]/59 mL; AVENA SATIVA FLOWERING TOP 10 [hp_X]/59 mL; BARIUM CARBONATE 10 [hp_X]/59 mL; BARIUM CHLORIDE DIHYDRATE 10 [hp_X]/59 mL; OYSTER SHELL CALCIUM CARBONATE, CRUDE 10 [hp_X]/59 mL; CALCIUM FLUORIDE 10 [hp_X]/59 mL; TRIBASIC CALCIUM PHOSPHATE 10 [hp_X]/59 mL; LYCOPODIUM CLAVATUM SPORE 10 [hp_X]/59 mL; THUJA OCCIDENTALIS LEAFY TWIG 10 [hp_X]/59 mL; BARIUM IODIDE 10 [hp_X]/59 mL
INACTIVE INGREDIENTS: WATER

Children's Growth and Development

Active Ingredients

Official HPUS: Alfalfa, Avena sativa, Baryta carbonica, Baryta muriatica, Baryta iodata, Calcarea carbonica, Calcarea fluorica, Calcarea phosphorica, Lycopodium clavatum, Thuja occidentalis

Reference image childrens growth.jpg

Inactive Ingredient

Equal volumes of each ingredient in a Bio-Energetically Enhanced pure water base: 10X, 30X, and LM1 potencies.

Reference image childrens growth.jpg

Purpose

Uses: To maximize children's growth potential and enhance development. Stimulates the body's ability to digest, absorb and use food. For maximum growth and development.

Dosage and administration

Directions: Initially, depress pump until primed. Hold close to mouth and spray directly into mouth. Use 3 times daily. Use additionally as needed.

Adult Dose- 3 pump sprays

Children 2-12- 2 pump sprays

Warnings

If symptoms persist or worsen, consult a physician. If pregnant or nursing, take only on advice of healthcare professional. Keep out of reach of children.

Other: Tamper resistant for your protection. Use only if safety seal is intact.

Keep out of reach of children.

Reference image childrens growth.jpg

Indications and Usage

To maximize children's growth potential and enhance development. Stimulates the body's ability to digest, absorb and use food. For maximum growth and development.

PACKAGE LABEL

King Bio Inc.

3 Westside Drive

Asheville, NC 28806

Questions? Call 800.543.3245

www.kingbio.com